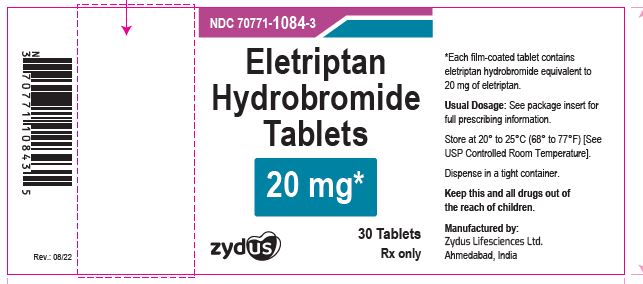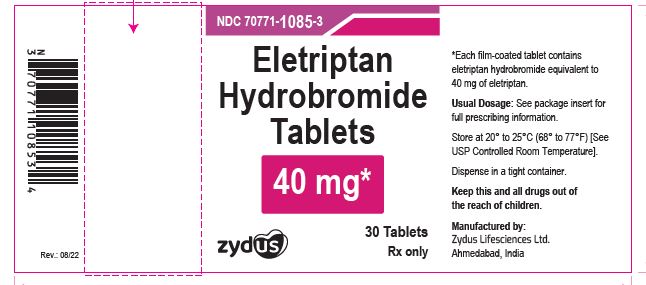 DRUG LABEL: Eletriptan hydrobromide
NDC: 70771-1107 | Form: TABLET, FILM COATED
Manufacturer: Zydus Lifesciences Limited
Category: prescription | Type: HUMAN PRESCRIPTION DRUG LABEL
Date: 20241128

ACTIVE INGREDIENTS: ELETRIPTAN HYDROBROMIDE 20 mg/1 1
INACTIVE INGREDIENTS: ANHYDROUS LACTOSE; CROSCARMELLOSE SODIUM; D&C YELLOW NO. 10; FD&C BLUE NO. 2--ALUMINUM LAKE; FD&C YELLOW NO. 6; HYPROMELLOSES; LACTOSE MONOHYDRATE; MAGNESIUM STEARATE; MICROCRYSTALLINE CELLULOSE 112; POVIDONE K30; TITANIUM DIOXIDE; TRIACETIN

ELETRIPTAN HYDROBROMIDE TABLETS

PACKAGE LABEL.PRINCIPAL DISPLAY PANEL

Eletriptan hydrobromide Tablets, 20 mg

NDC 70771-1107-3

Rx only

30 Tablets

Eletriptan hydrobromide Tablets, 40 mg

NDC 70771-1108-3

Rx only

30 Tablets